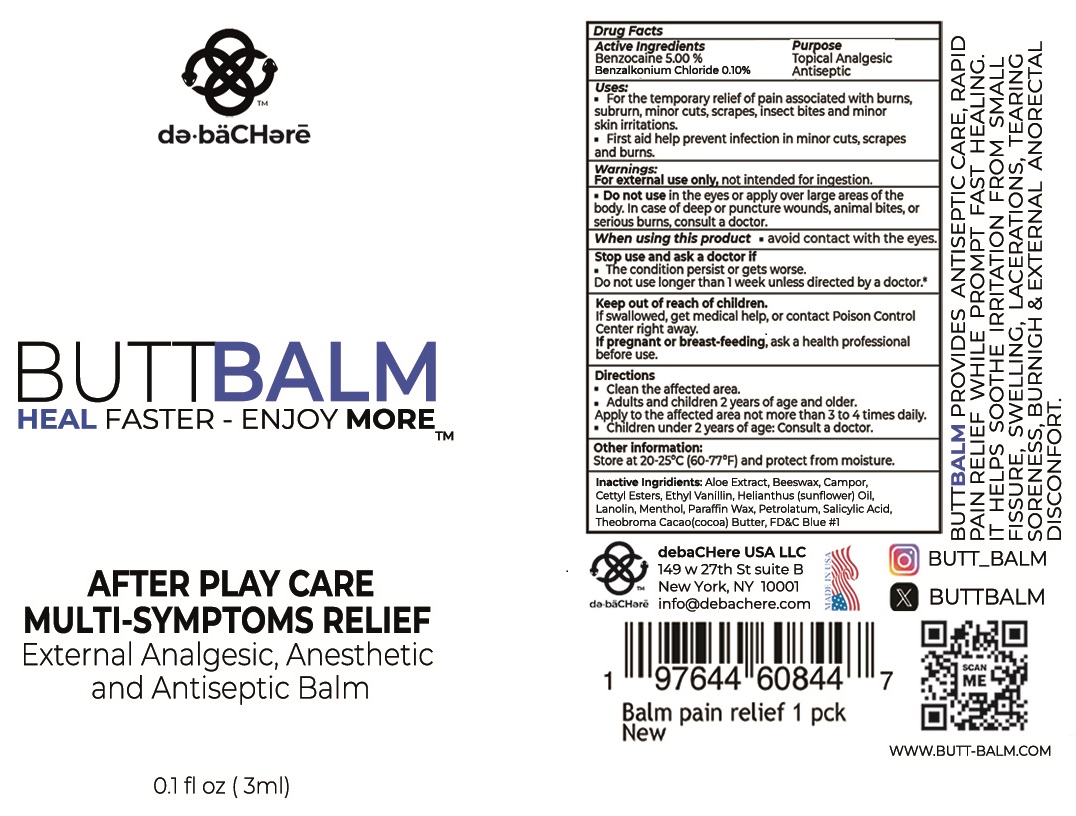 DRUG LABEL: DEBACHERE Butt Balm After Play Care Multi Symptoms Relief
NDC: 84847-940 | Form: CREAM
Manufacturer: DE.BACHERE USA LLC
Category: otc | Type: HUMAN OTC DRUG LABEL
Date: 20250317

ACTIVE INGREDIENTS: BENZOCAINE 50 mg/1 mL; BENZALKONIUM CHLORIDE 10 mg/1 mL
INACTIVE INGREDIENTS: ALOE VERA LEAF; YELLOW WAX; CETYL ESTERS WAX; ETHYL VANILLIN; HELIANTHUS ANNUUS FLOWERING TOP; LANOLIN; MENTHOL; PARAFFIN; PETROLATUM; SALICYLIC ACID; COCOA; FD&C BLUE NO. 1

DEBACHERE Butt Balm After Play Care Multi Symptoms Relief

Active ingredients

Benzocaine 5.00%
Benzalkonium Chloride 0.10%

Purpose

Topical Analgesic

Antiseptic

Uses:

- For the temporary relief of pains associated with burns, subrurn, minor cuts, scrapes, insect bites and minor skin irritations.
- First aid help prevent infection in minor cuts, scrapes and burns.

Warnings:

For external use only, not intended for ingestion.

Do not use

- in the eyes or apply over large areas of the body. In case of deep or puncture wounds, animal bites, or serious burns, consult a doctor.

When using this product

- avoid contact with the eyes.

Stop use and ask a doctor if

- The condition persists or gets worse.

Do not use longer than 1 week unless directed by a doctor.

Keep out of reach of children.

If swallowed, get medical help, or contact Poison Control Center right away.

If pregnant or breast-feeding,

ask a health professional before use.

Directions

- Clean the affected area.
- Adults and children 2 years of age and older. Apply to affected area not more than 3 to 4 times daily.
- Children under 2 years of age: Consult a doctor.

Other information:

- Store at 20-25°C (60-77°F) and protect from moisture.

Inactive Ingredients

Aloe Extract, Beeswax, Campor, Cetty Esters, Ethyl Vanillin, Helianthus (sunflower) Oil, Lanolin, Menthol, Paraffin Wax, Petrolatum, Salicylic Acid, Theobroma Cacao(cocoa) Butter, FD&C Blue #1